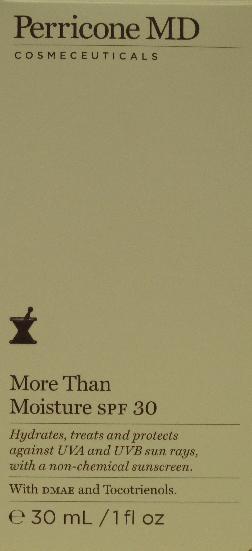 DRUG LABEL: More Than Moisture SPF 30
NDC: 62742-4049 | Form: CREAM
Manufacturer: Allure Labs, Inc.
Category: otc | Type: HUMAN OTC DRUG LABEL
Date: 20100803

ACTIVE INGREDIENTS: ZINC OXIDE 105 mg/1 mL

Drug Facts

ACTIVE INGREDIENT:
Zinc Oxide 10.5%

PURPOSE:
Sunscreen

USES:

- Helps prevent sunburn.
- Higher SPF gives more sunburn protection.

WARNINGS:

- For external use only.

WHEN USING THIS PRODUCT:

- Keep out of eyes. Rinse with water to remove.

STOP USE AND ASK A DOCTOR IF

- Rash or irritation develops and lasts.

KEEP OUT OF REACH OF CHILDREN
If swallowed, get medical help or contact a Poison Control Center right away.

DIRECTIONS:

- Dr. Perricone recommends applying liberally on cleaned skin or on top of treatment every 2 hours before sun exposure and as needed. For children under 6 years old, consult a doctor before use.

OTHER INFORMATION:

- Store at room temperature.
- Sun alert: Limiting sun exposure, wearing protective clothing, and using sunscreen may reduce the risk of skin aging, skin cancer, and other harmful effects of the sun.

INACTIVE INGREDIENTS:

Aqua (Water), Dimethicone, Olea Europaea (Olive) Fruit Oil, Glycerin, Cyclopentasiloxane, Seareth-20, Stearyl Alcohol, Tetrahexyldecyl Ascorbate, PPG-3 Benzyl Ether Myristate, Neopentyl Glycol Diheptanoate, C12-15 Alkyl Benzoate, Cetyl Palmitate, Butyropsermum Parkii (Shea Butter), Citrus Paradisi (Grape Fruit) Oil, Prunus Armeniaca (Apricot) Kernel oil, Sorbitan Palmitate, Sorbitan Olivate, Cyclohexasiloxane, Dimethyl MEA (DMAE), Squalane, Xanthan Gum, Phenoxyethanol, Carthamus Tinctorius (Safflower) Seed Oil, Perfume (Fragrance), Caprylyl Glycol, Tocopheryl Acetate, Limonene, Triethoxycaprylylsilane, Galactoarabina, Propylne Glycol, Olea Europaea (Olive) Leaf Extract, Ethylhexylglycerin, Hexylene Glycol, Thioctic Acid (Alpha-Lipoic Acid), Ubiquinone, Disodium EDTA, Aloe Barbadensis Leaf Extract, Chamomilla Recutita (Matricaria) Extract, Magnesium Aspartate, Zinc Gluconate, Hydrolyzed Glycosaminoglycans, Elaeis Guineensis (Palm)oil, Tocotrienols, Camellia Sinensis (Green Tea) Leaf Extract, Titanium Dioxide, Vanilla Planifolia Fruit Extract, Vanillin, Tocopherol, Copper Gluconate, Sodium Hyaluronate, Linalool, Aluminum Hydroxide, Stearic Acid.

PACKAGE LABEL

DISTRIBUTED BY:

US:

NV Perricone LLC,

Meriden CT 06450

USA

UK:

NV Perricone MD Cosmeceuticals LTD,

London, W1S 2YE UK

IMAGE OF THE PRINCIPAL DISPLAY PANEL: